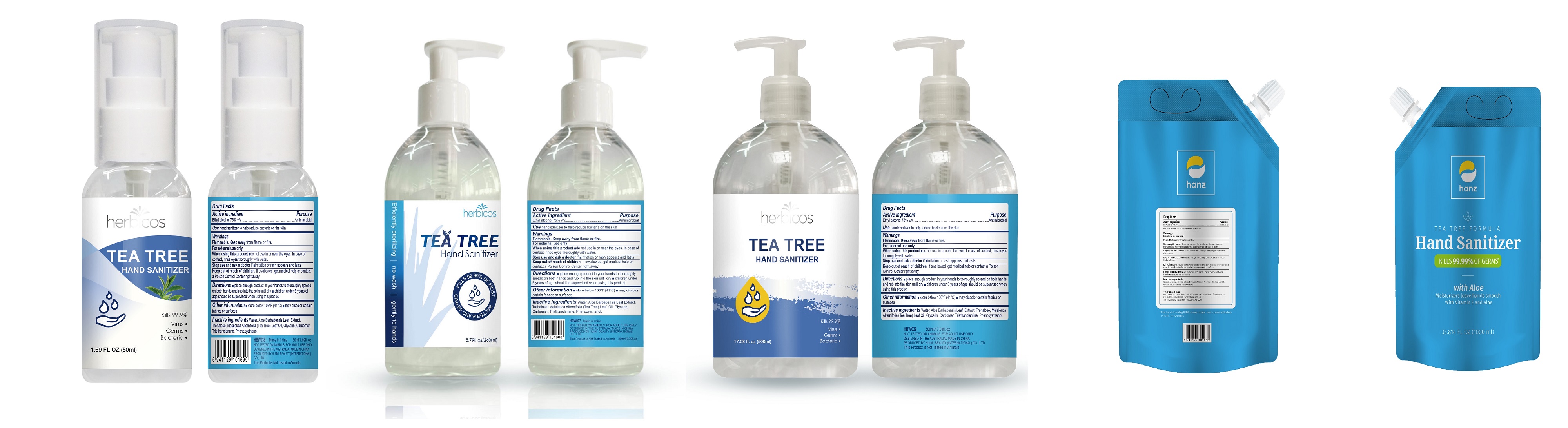 DRUG LABEL: Tea Tree Hand Sanitizer
NDC: 75713-005 | Form: LIQUID
Manufacturer: Guangzhou Meisheng Cosmetic Co. Ltd.
Category: otc | Type: HUMAN OTC DRUG LABEL
Date: 20200422

ACTIVE INGREDIENTS: ALCOHOL 75 mL/100 mL
INACTIVE INGREDIENTS: ALOE VERA LEAF; MELALEUCA ALTERNIFOLIA LEAF; PHENOXYETHANOL; TREHALOSE; TROLAMINE; GLYCERIN; CARBOMER 934; WATER

Tea Tree Hand Sanitizer

Active Ingredient

Ethyl alcohol 75% V/V

Purpose

Antimicrobial

Use

hand sanitizer to help reduce bacteria on the skin

Warnings

Flammable. Keep away from flame or fire.For external use only

When using this product ado not use in or near the eyes, In case of contact, rinse eyes.thoroughly with water

Stop use and ask a doctor if imitation or rash appears and lasts

Keep out of reach of children. If swallowed, get medical help or contact a Poison Control Center right away

Directions

place enough product in your hands to thoroughly spread on both hand sand rub into the skin until dry m children under 6 years of age should be supervised when using this product

Other information

store below 106F(41 C)

may discolor certain fabrics or surfaces

Inactive ingredients

Water, Aloe Barbadensis Leaf Extract, Trehalose, Melaleuca Alternifolia (Tea Tree)Leaf Oil, Glycerin, Carbomer, Triethanolamine, Phenoxyethanol